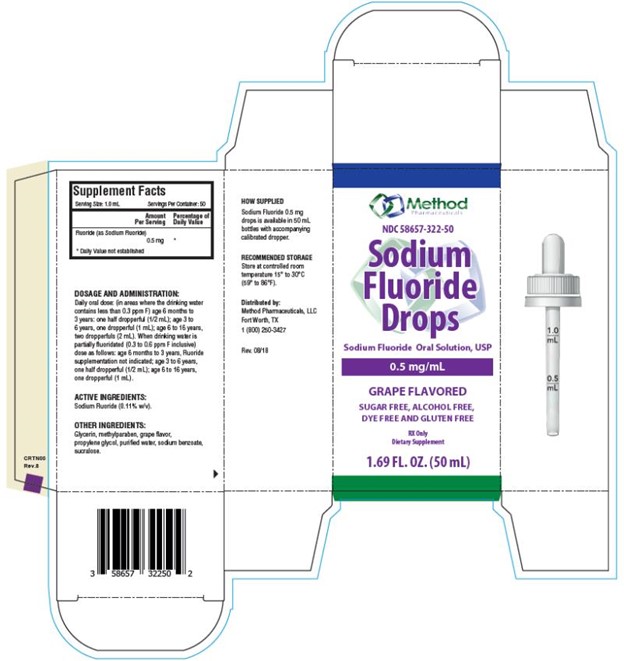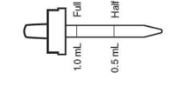 DRUG LABEL: Sodium Fluoride
NDC: 58657-322 | Form: SOLUTION/ DROPS
Manufacturer: Method Pharmaceuticals, LLC
Category: prescription | Type: HUMAN PRESCRIPTION DRUG LABEL
Date: 20251021

ACTIVE INGREDIENTS: SODIUM FLUORIDE 0.5 mg/1 mL
INACTIVE INGREDIENTS: GLYCERIN; METHYLPARABEN; PROPYLENE GLYCOL; WATER; SODIUM BENZOATE; SUCRALOSE

Sodium Fluoride Drops

SODIUM FLUORIDE- sodium fluoride solution/ drops

Sodium Fluoride Drops 0.5 mg/mL

GRAPE FLAVORED

Description

Each mL of Sodium Fluoride Drops contains 0.5 mg Fluoride ion (F) from 1.1 mg Sodium Fluoride (NaF). For use as a dental caries preventive in pediatric patients. Sugar Free, Alcohol Free, Dye Free and Gluten Free.

Supplement Facts

Serving Size: 1 mL

Servings Per Container: 50

Amount per serving % Daily Value

Fluoride (as Sodium Fluoride) 0.5 mg **

** Daily Value not established.

Active Ingredients: Sodium Fluoride (0.11% w/v).

Other Ingredients: Glycerin, methylparaben, grape flavor, propylene glycol, purified water, sodium benzoate, sucralose.

FLUORIDE SUPPLEMENT DOSAGE SCHEDULES
AGE | Fluoride Ion Level in Drinking Water (ppm)*
 | < 0.3 ppm | 0.3 - 0.6 ppm | > 0.6 ppm
Birth to 6 months | None | None | None
6 months to 3 years | Half dropperful 0.25 mg F (1/2 mL) | None | None
3 to 6 years | One dropperful 0.5 mg F (1 mL)† | Half dropperful 0.25 mg F (1/2 mL) | None
6 to 16 years | Two dropperfuls 1 mg F (2 mL) | One dropperful 0.5 mg F (1 mL) | None

* 1.0 ppm = 1 mg/Liter

† 1.1 mg Sodium Fluoride contains 0.5 mg Fluoride ion

Fluoride Supplement Dose Schedule approved by the American Dental Association, American Academy of Pediatrics and American Academy of Pediatric Dentistry.

KEEP THIS AND ALL MEDICATIONS OUT OF THE REACH OF CHILDREN.

Clinical Pharmacology

Sodium Fluoride acts systemically (before tooth eruption) and topically (post eruption) by increasing tooth resistance to acid dissolution, by promoting remineralization and by inhibiting the cariogenic microbial process.

Indications and Usage

As a supplemental source of Fluoride. It has been established that ingestion of fluoridated drinking water (1 ppm F) during the period of tooth development results in significant decrease in the incidence of dental caries.1 Sodium Fluoride Drops were developed to provide systemic Fluoride for use as a supplement

in pediatric patients from 6 months to age 3 and older, living in areas where the drinking water Fluoride level does not exceed 0.6 ppm F.

Contraindications

Do not use in areas where drinking water exceeds 0.6 ppm F. Do not administer to pediatric patients less than 6 months old.

Warnings

Prolonged daily ingestion of quantities greater than the recommended amount may result in various degrees of dental fluorosis in pediatric patients under age 6 years, especially if the water fluoridation exceeds 0.6 ppm. Read directions carefully before using. Keep out of the reach of infants and children.

Precautions

See " Overdosage" section. Incompatibility of Fluoride with dairy foods has been reported due to formation of Calcium Fluoride which is poorly absorbed. Not for use in the eyes.

Adverse Reactions

Allergic rash and other idiosyncrasies have been rarely reported.

To report SUSPECTED ADVERSE REACTIONS, contact the FDA at 1-800-FDA-1088 or Method Pharmaceuticals, LLC at 877-250-3427.

Store at controlled room temperature 15° to 30°C (59° to 86°F).

Overdosage

Prolonged daily ingestion of excessive Fluoride may result in varying degrees of dental fluorosis. The total amount of Sodium Fluoride in a bottle of 50 mL (0.5 mg/mL) Sodium Fluoride Drops (25 mg F) conforms with the recommendations of the American Dental Association for the maximum to be dispensed at one time for safety purposes. If overdose is suspected, call 1-800-222-1222 (American Association of Poison Control Centers), your local poison control center (www.aapcc.org), or emergency room immediately for treatment recommendations.

Dosages and Administration

Daily oral dose: (in areas where the drinking water contains less than 0.3 ppm F) age 6 months to 3 years: one half dropperful (1/2 mL); age 3 to 6 years, one dropperful (1 mL); age 6 to 16 years, two dropperfuls (2 mL). When drinking water is partially fluoridated (0.3 to 0.6 ppm F inclusive) dose as follows: age 6 months to 3 years, Fluoride supplementation not indicated; age 3 to 6 years, one half dropperful (1/2 mL); age 6 to 16 years, one dropperful (1 mL).

How Supplied

50 mL bottles (58657-322-50)

References

1. Accepted Dental Therapeutics, Ed. 40. American Dental

Association, Chicago, 1984:399-402.

2. Jakush, J, New Fluoride Schedule Adopted. ADA News.

May 16, 1994:12-14.

Manufactured by:

Method Pharmaceuticals, LLC
Fort Worth, TX 76118

Rev. 07/2018

PRINCIPAL DISPLAY PANEL

NDC 58657-322-50
Sodium
Fluoride
Drops
Sodium Fluoride Oral Solution, USP
0.5 mg/mL
GRAPE FLAVORED
1.69 FL. OZ. (50 mL)